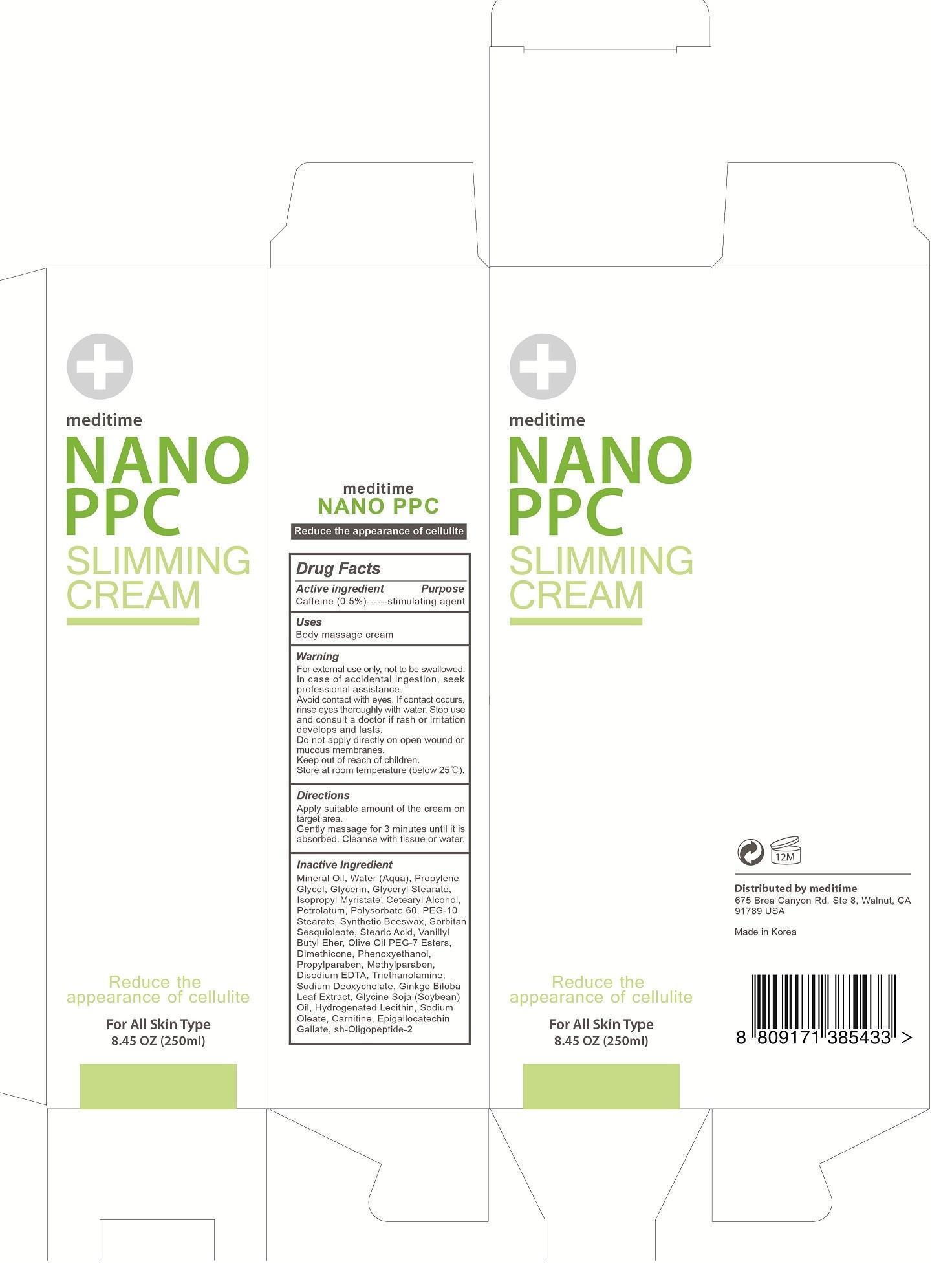 DRUG LABEL: NANO PPC
NDC: 60709-107 | Form: CREAM
Manufacturer: YBK Investment, INC
Category: otc | Type: HUMAN OTC DRUG LABEL
Date: 20131211

ACTIVE INGREDIENTS: VANILLYL BUTYL ETHER 2.50 mg/250 mL; CAFFEINE 1.25 mg/250 mL
INACTIVE INGREDIENTS: MINERAL OIL 90.00 mg/250 mL; water 84.928 mg/250 mL; PROPYLENE GLYCOL 17.50 mg/250 mL; GLYCERIN 12.50 mg/250 mL; GLYCERYL STEARATE SE 6.875 mg/250 mL; ISOPROPYL MYRISTATE 6.25 mg/250 mL; CETOSTEARYL ALCOHOL 3.75 mg/250 mL; PETROLATUM 3.75 mg/250 mL; POLYSORBATE 60 3.75 mg/250 mL; PEG-100 STEARATE 3.125 mg/250 mL; YELLOW WAX 3.00 mg/250 mL; SORBITAN SESQUIOLEATE 3.00 mg/250 mL; STEARIC ACID 2.50 mg/250 mL; OLIVE OIL 2.00 mg/250 mL; DIMETHICONE 1.25 mg/250 mL; PHENOXYETHANOL 0.75 mg/250 mL; PROPYLPARABEN 0.50 mg/250 mL; METHYLPARABEN 0.50 mg/250 mL; EDETATE DISODIUM 0.125 mg/250 mL; TROLAMINE 0.125 mg/250 mL; SODIUM DESOXYCHOLATE 0.030 mg/250 mL; GINKGO BILOBA LEAF OIL 0.025 mg/250 mL; SOYBEAN OIL 0.010 mg/250 mL; HYDROGENATED SOYBEAN LECITHIN 0.005 mg/250 mL; SODIUM OLEATE 0.001 mg/250 mL; CARNITINE 0.00025 mg/250 mL; EPIGALLOCATECHIN GALLATE 0.00025 mg/250 mL; MECASERMIN 0.0000375 mg/250 mL

NANO-PPC 250mL

NANO-PPC massage and slimming cream

Active ingredients: Caffeine (0.5%)

Reduce the appearance of cellulite

Inactive ingredients:

Water, Mineral oil, Propylene glycol, Glycerin, Glyceryl stearate, Stearic acid, isopropyl myristate, Petrolatum, Polysorbate 60, Cetyl alcohol, Olea europaea (olive) fruit oil, Sorbitan sesquioleate, Dimethicone, Potassium acetyl phosphate, Methylparaben, Sodium lauryl glutamate, Carbomer, Triethanolamine, Imidazolidinyl urea, Propylparaben, Butylated hydroxytoluene, Disodium EDTA, Glycine soja (soybean) oil, Hydrogenated lecithin, Carnitine

Active ingredients: Caffeine (0.5%)

Keep out of reach of children

INDICATIONS AND USAGE

Direction for use

Apply suitable amount of the cream on target area.

Gently massage for 3 minutes until it is absorbed. Cleanse with tissue or water.

WARNINGS

Cautions

For external use only, not to be swallowed. In case of accidental ingestion, seek professional assistance. Avoid contact with eyes. If contact occurs, rinse eyes thoroughly with water. Do not apply directly to wound or open cut. Store at room temperature

PURPOSE

Reduce the appearance of cellulite

Inactive ingredients:

Water, Mineral oil, Propylene glycol, Glycerin, Glyceryl stearate, Stearic acid, isopropyl myristate, Petrolatum, Polysorbate 60, Cetyl alcohol, Olea europaea (olive) fruit oil, Sorbitan sesquioleate, Dimethicone, Potassium acetyl phosphate, Methylparaben, Sodium lauryl glutamate, Carbomer, Triethanolamine, Imidazolidinyl urea, Propylparaben, Butylated hydroxytoluene, Disodium EDTA, Glycine soja (soybean) oil, Hydrogenated lecithin, Carnitine

DOSAGE AND ADMINISTRATION

massage skin

reduce the appearance of cellulite

Stop use and consult a doctor if rash or irritation develops and lasts.

WARNINGS AND PRECAUTIONS

Cautions

For external use only, not to be swallowed. In case of accidental ingestion, seek professional assistance. Avoid contact with eyes. If contact occurs, rinse eyes thoroughly with water. Do not apply directly to wound or open cut. Store at room temperature